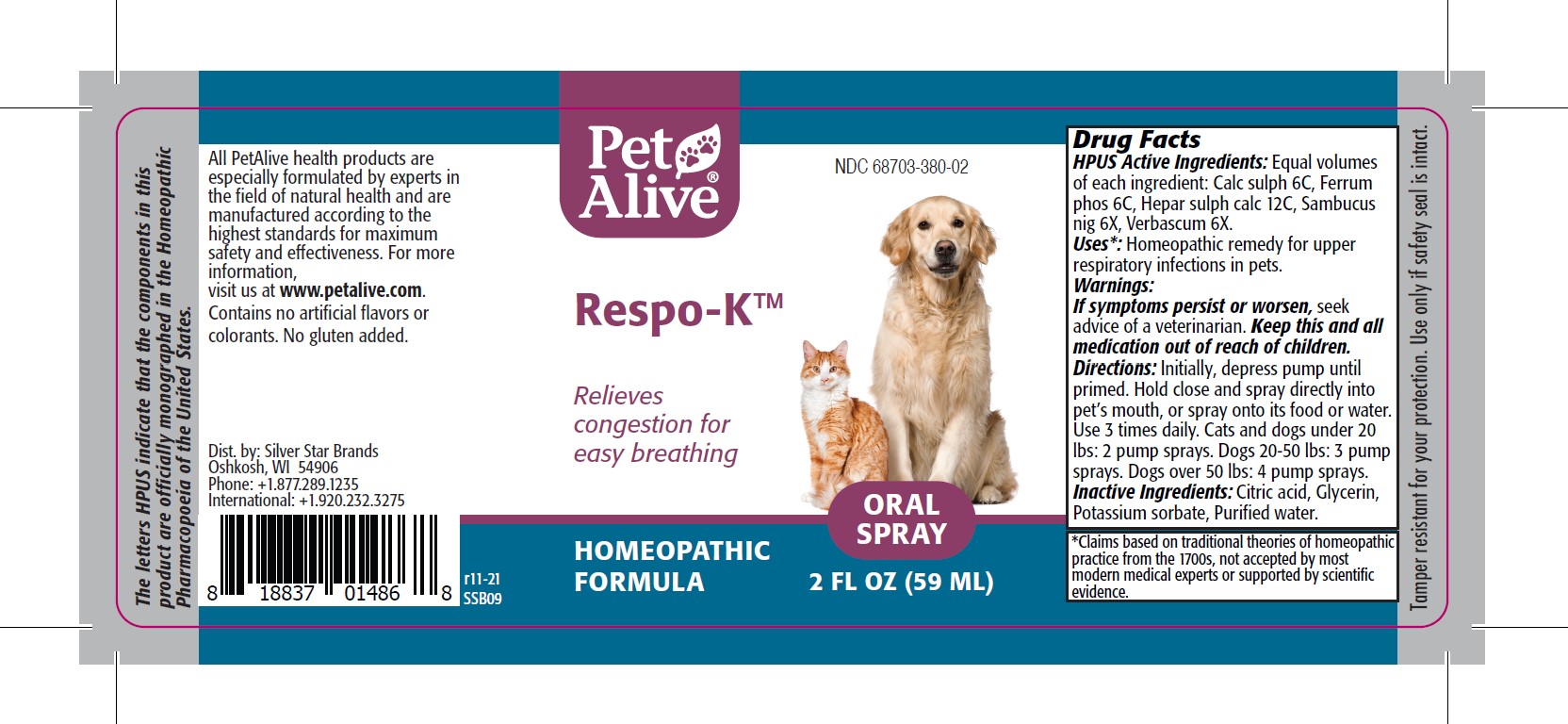 DRUG LABEL: PetAlive Respo-K
NDC: 68703-380 | Form: SPRAY
Manufacturer: SILVER STAR BRANDS
Category: homeopathic | Type: OTC ANIMAL DRUG LABEL
Date: 20251216

ACTIVE INGREDIENTS: CALCIUM SULFATE ANHYDROUS 6 [hp_C]/59 mL; FERROSOFERRIC PHOSPHATE 6 [hp_C]/59 mL; CALCIUM SULFIDE 12 [hp_C]/59 mL; SAMBUCUS NIGRA FLOWERING TOP 6 [hp_X]/59 mL; VERBASCUM THAPSUS 6 [hp_X]/59 mL
INACTIVE INGREDIENTS: CITRIC ACID MONOHYDRATE; GLYCERIN; POTASSIUM SORBATE; WATER

PetAlive Respo-K

PURPOSE

Relieves congestion for easy breathing

HPUS Active Ingredients:

Calc sulph 6C
Ferrum phos 6C
Hepar sulph calc 12C
Sambucus nig 6X
Verbascum 6X

INDICATIONS AND USAGE

Uses: Homeopathic remedy for upper respiratory infections in pets.

WARNINGS

Warnings: If symptoms persist of worsen, seek advice of a veterinariam.

KEEP OUT OF REACH OF CHILDREN

Keep this and all medication out of reach of children.

DOSAGE AND ADMINISTRATION

Directions: Initially, depress pump until primed. Hold close and spray directly into pet's mouth, or spray onto its food or water. Use 3 times daily. Cats and dogs under 20 lbs: 2 pump sprays. Dogs 20-50 lbs: 3 pump sprays. Dogs over 50 lbs: 4 pump sprays.

INACTIVE INGREDIENT

Inactive Ingredients: Citric Acid, Glycerin, Potassium sorbate, Purified water

INFORMATION FOR OWNERS/CAREGIVERS

The letters HPUS indicate that the components in this product are officially monographed in the Homeopathic Pharmacopoeia of the United States.

All PetAlive health products are especially formulated by experts in the field of natural health and are manufactured according to the highest standards for maximum safety and effectiveness. For more information, visit us at www.petalive.com.

Contains no artificial flavors or colorants. No gluten added.

Distributed by: Silver Star Brands
Oshkosh, WI 54906
Phone: +1.877.289.1235
International: +1.920.232.3275

STORAGE AND HANDLING

Tamper resistant for your protection. Use only if safety seal is intact